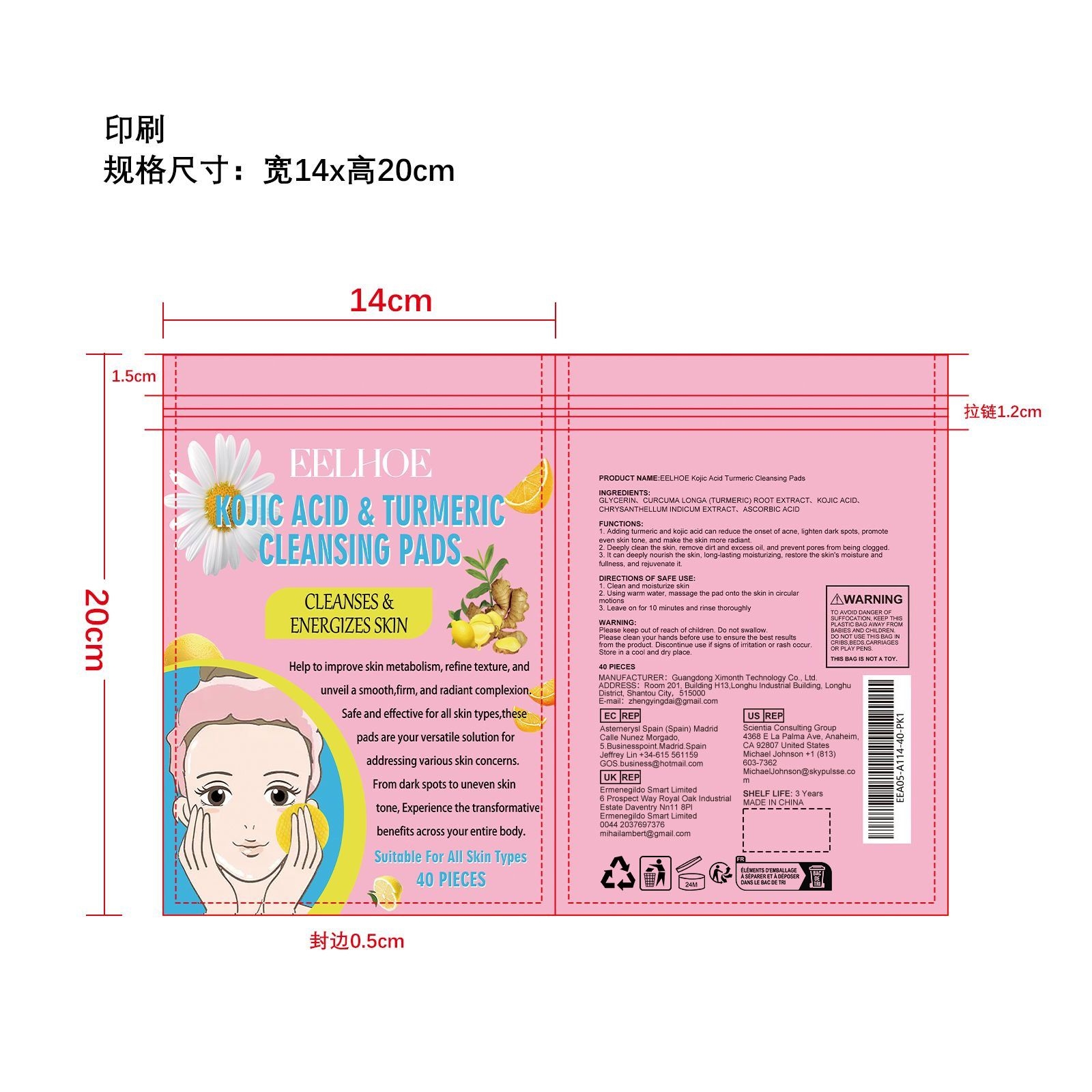 DRUG LABEL: EELHOE Kojic Acid Turmeric Cleansing Pads
NDC: 84660-023 | Form: PATCH
Manufacturer: Guangdong Ximonth Technology Co., Ltd.
Category: otc | Type: HUMAN OTC DRUG LABEL
Date: 20240924

ACTIVE INGREDIENTS: TURMERIC 14.5 g/58 g; KOJIC ACID 11.6 g/58 g; CHRYSANTHELLUM INDICUM TOP 8.7 g/58 g
INACTIVE INGREDIENTS: ASCORBIC ACID 5.8 g/58 g; GLYCERIN 17.4 g/58 g

Active Ingredient(s)

CURCUMA LONGA (TURMERIC) ROOT EXTRACT、KOJIC ACID、CHRYSANTHELLUM INDICUM EXTRACT、ASCORBIC ACID

Purpose

1. Adding turmeric and kojic acid can reduce the onset of acne, lighten dark spots,promote even skin tone, and make the skin more radiant.
2. Deeply clean the skin, remove dirt and excess oil, and prevent pores from being clogged.
3. It can deeply nourish the skin, long-lasting moisturizing, restore the skin's moisture and fullness, andrejuvenate it.

Use

1. Clean and moisturize skin
2. Using warm water, massage the pad onto the skin in circular motions
3. Leave on for 10 minutes and rinse thoroughly

Warnings

Please keep out of reach of children.Do not swallow.Please clean your hands before use to ensure the best results from the product.Discontinue use if signs of irritation or rash occur.Store in a cool and dry place.

STOP USE

Discontinue use if signs of irritation or rash occur.

KEEP OUT OF REACH OF CHILDREN

Please keep out of reach of children. Do not swallow

STORAGE AND HANDLING

Avoid freezing and excessive heat above 40C (104F) ）
Store in a cool and dry place.

INACTIVE INGREDIENT

GLYCERIN

Do not use

Discontinue use if signs of irritation or rash occur